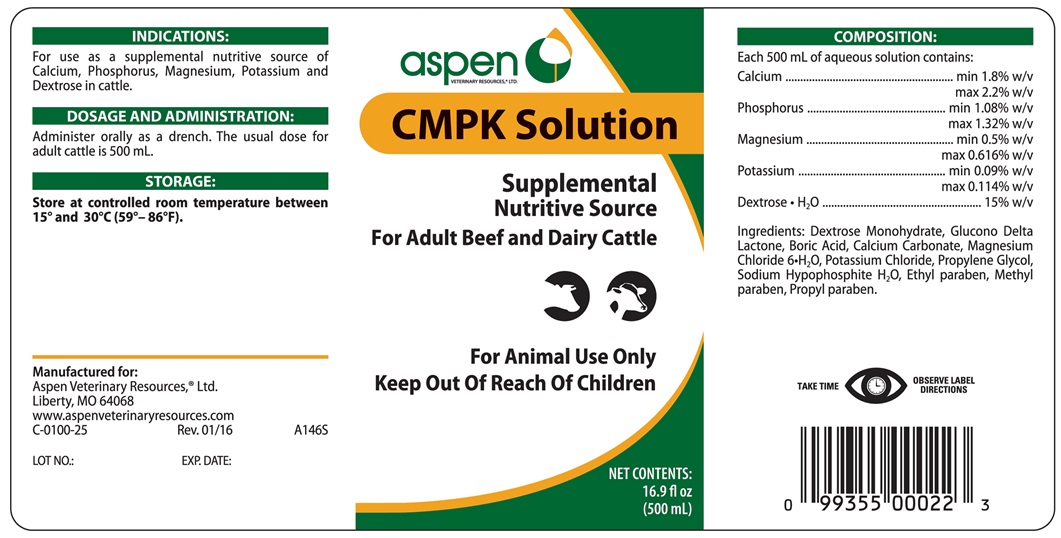 DRUG LABEL: CMPK
NDC: 46066-219 | Form: SOLUTION
Manufacturer: Aspen Veterinary Resources, Ltd.
Category: animal | Type: OTC ANIMAL DRUG LABEL
Date: 20180426

ACTIVE INGREDIENTS: CALCIUM CARBONATE 9 g/500 mL; SODIUM HYPOPHOSPHITE MONOHYDRATE 5.4 g/500 mL; MAGNESIUM CHLORIDE 2.5 g/500 mL; POTASSIUM CHLORIDE 0.45 g/500 mL; DEXTROSE MONOHYDRATE 75 g/500 mL

CMPK Solution

INDICATIONS AND USAGE

Supplemental Nutritive Source

For Adult Beef and Dairy Cattle

For Animal Use Only

Keep Out of Reach of Children

INDICATIONS

For use as a supplemental nutritive source of Calcium, Phosphorus, Magnesium, Potassium and Dextrose in cattle.

DOSAGE AND ADMINISTRATION

Administer orally as a drench. The usual dose for adult cattle is 500 mL.

STORAGE AND HANDLING

Store at controlled room temperature between 15° and 30°C (59°-86°F)

TAKE TIME OBSERVE LABEL DIRECTIONS

COMPOSITION

Each 500 mL of aqueous solution contains:

Calcium ............................... min 1.8% w/v, max 2.2% w/v

Phosphorus ...................... min 1.08% w/v, max 1.32% w/v

Magnesium ...................... min 0.5% w/v, max 0.616% w/v

Potassium ...................... min 0.09% w/v, max 0.114% w/v

Dextrose·H2O ................................................... 15% w/v

Ingredients: Dextrose Monohydrate, Glucono Delta Lactone, Boric Acid, Calcium Carbonate, Magnesium Chloride 6·H2O, Potassium Chloride, Propylene Glycol, Sodium Hypophosphite H2O, Ethyl Paraben, Methyl Paraben and Propyl Paraben.